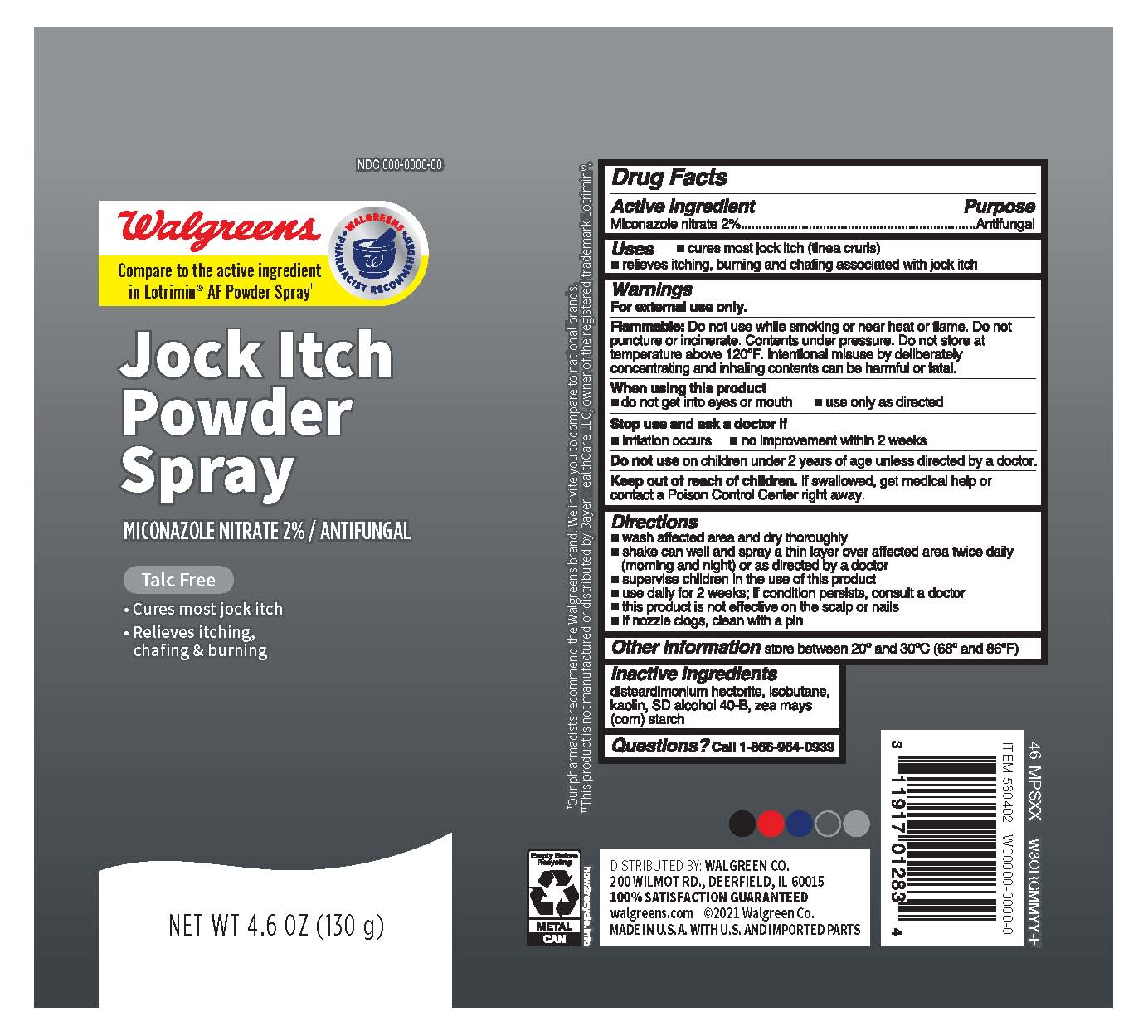 DRUG LABEL: Miconazole Nitrate 2%
NDC: 0363-5353 | Form: AEROSOL, SPRAY
Manufacturer: Walgreens Company
Category: otc | Type: HUMAN OTC DRUG LABEL
Date: 20251106

ACTIVE INGREDIENTS: MICONAZOLE NITRATE 1.3 g/131 g
INACTIVE INGREDIENTS: STARCH, CORN; ALCOHOL; ISOBUTANE; KAOLIN; DISTEARDIMONIUM HECTORITE

Walgreens Jock Itch Powder Spray

Active ingredient

Miconazole nitrate 2%

Purpose

Antifungal

Uses

- cures most jock itch (tinea cruris)
- relieves itching, burning and chafing associated with jock itch

Warnings

For external use only.

Flammable:

Do not use while smoking or near heat or flame. Do not puncture or incinerate. Contents under pressure. Do not store at temperature above 120ºF. Intentional misuse by deliberately concentrating and inhaling contents can be harmful or fatal.

When using this product

- do not get into eyes or mouth
- use only as directed

Stop use and ask a doctor if

- irritation occurs
- no improvement within 2 weeks

Do not use

on children under 2 years of age unless directed by a doctor.

Keep out of the reach of children.

If swallowed, get medical help or contact a Poison Control Center right away.

Directions

- wash affected area and dry thoroughly
- shake can well and spray a thin layer over affected area twice daily (morning and night) or as directed by a doctor
- supervise children in the use of this product
- use daily for 2 weeks; if condition persists, consult a doctor
- this product is not effective on the scalp or nails
- if nozzle clogs, clean with a pin

Other Information

store between 20º and 30ºC (68º and 86ºF)

Inactive ingredients

disteardimonium hectorite, isobutane, kaolin, SD alcohol 40-B, zea mays (corn) starch

Questions?

Call 1-866-964-0939

Principal Display Panel

ANTIFUNGAL

Jock Itch

Powder Spray

Miconazole Nitrate 2%

- Cures most jock itch
- Relieves itching, chafing and burning
- Talc-free

NET WT 4.6 OZ (130g)